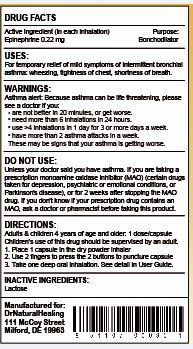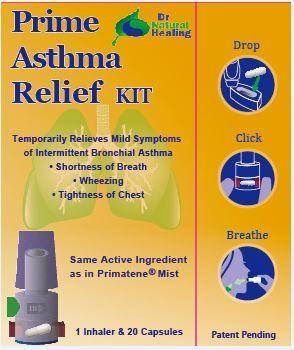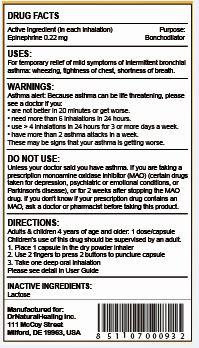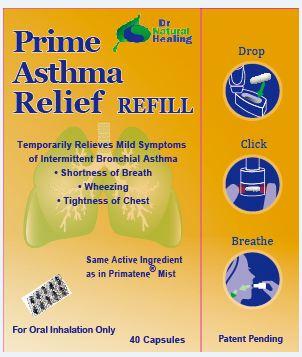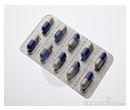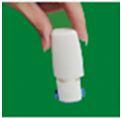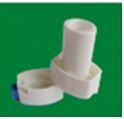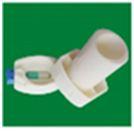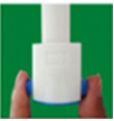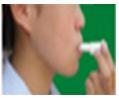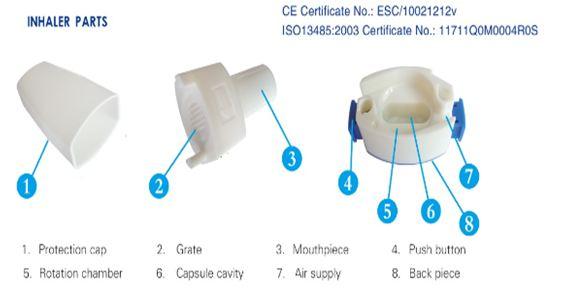 DRUG LABEL: PRIME ASTHMA RELIEF
NDC: 15343-105 | Form: CAPSULE
Manufacturer: DRNATURALHEALING
Category: otc | Type: HUMAN OTC DRUG LABEL
Date: 20140619

ACTIVE INGREDIENTS: EPINEPHRINE 0.22 mg/1 1
INACTIVE INGREDIENTS: LACTOSE 49.78 mg/1 1

ACTIVE INGREDIENT

Epinephrine, USP 0.22 mg per capsule/dose

PURPOSE

Bronchodilator

USE

For temporary relief of mild symptoms of intermittent asthma:

- wheezing
- tightness of chest
- shortness of breath

WARNINGS

Asthma Alert:
Because asthma may be life threatening, see a doctor if you:

- are not better in 20 minutes
- get worse
- need more than 6 inhalations in 24 hours
- use more than 4 inhalations in 24 hours for 3 or more days a week
- have more than 2 asthma attacks in a week

These may be signs that your asthma is getting worse

Do not use

- unless a doctor said you have asthma
- if you are now taking a prescription monoamine oxidase inhibitor (MAOI) (certain drugs taken for depression, psychiatric or emotional conditions, or Parkinson’s disease), or for 2 weeks after stopping the MAOI drug. If you do not know if your prescription drug contains an MAOI, ask a doctor or pharmacist before taking this product.

Ask a doctor before use if you have:

- ever been hospitalized for asthma
- heart disease
- high blood pressure
- diabetes
- thyroid disease
- seizures
- narrow angle glaucoma
- a psychiatric or emotional condition
- trouble urinating due to an enlarged prostate gland

Ask a doctor or pharmacist before use if you are

- taking prescription drugs for asthma, obesity, weight control, depression, or psychiatric or emotional conditions
- taking any drug that contains phenylephrine, pseudoephedrine, ephedrine, or caffeine (such as for allergy, cough-cold, or pain)

When using this product

- your blood pressure or heart rate may go up. This could increase your risk of heart attack or stroke, which may cause death.
- Your risk of heart attack or stroke increases if you:
  - have a history of high blood pressure or heart disease
  - take this product more frequently or take more than the recommended dose
- avoid foods or beverages that contain caffeine
- avoid dietary supplements containing ingredients reported or claimed to have a stimulant effect

Stop use and ask doctor if

- your asthma is getting worse (see Asthma alert)
- you have difficulty sleeping
- you have a rapid heartbeat
- you have tremors, nervousness, or seizure

PREGNANCY OR BREAST FEEDING

If pregnant or breast-feeding, ask a health professional before use.

Keep out of reach of children. In case of overdose, get medical help or contact a Poison Control Center right away.

DIRECTIONS:

- do not use more than directed
- adults and children 4 years of age and over: 1 capsule is for one inhalation at one time
- inhalation not more often than every 3 hours
- do not use more than 12 inhalations in 24 hours
- the use of this product by children should be supervised by an adult
- children under 4 years of age: ask a doctor

1) The active ingredient in a dry powder is 0.22 mg per capsule (the concentration is 1% epinephrine in the total weight of the dry powder)

2) For use in a dry powder inhaler for holding the No. 3 capsule.

3) Should orally inhale at least two times after the capsule is pierced to make sure all dry powder is inhaled into the lung

4) Instructions for Inhalation:
A. Inhaler parts:

B. Instructions for using the dry powder inhaler:
Wash and dry your hands completely before touching the inhaler and capsule.
(1) Remove the cap.
(2) Hold the inhaler at base and turn the mouthpiece in direction of the arrow.
(3) Obtain 1 capsule from the blister package just prior to use.
(4) Open inhaler by turning mouthpiece as indicated. Load 1 capsule in the capsule-chamber of the inhaler. Do not put the capsule directly into the top of the mouthpiece. Twist the mouthpiece to the closed position.
(5) Hold the inhaler upright, push/click two blue buttons inwards all the way. Let go of the blue buttons. Do not press the blue buttons more than 1 time. The chances of the capsule breaking into pieces will be increased if the capsule is accidentally pierced more than once.
(6) With the inhaler away from your mouth, prepare by breathing out (exhaling) all the way. Do not blow or exhale into the mouthpiece.
(7) Hold the inhaler horizontally. Place your mouth over the mouthpiece and close your lips tightly around it. Inhale quickly and deeply.
(8) Hold your breath for count of ten, or as long as is comfortable. Breathe out gently. You will need to inhale at least twice from one capsule in order to get the full dose.
(9) After the dose, open the mouthpiece, remove the used capsule, and take a look at the used capsule. It should be pierced and empty. If so, dispose of it properly. If the capsule does not look pierced, put the capsule back into the device capsule-chamber, repeat steps 7, 8 and 9.
(10) Cover the mouthpiece and dust cap for storage.
(11) After your Inhalation, throw away the empty capsule properly as it is bio-degradable. Do not store the capsule in the inhaler. Put the mouthpiece back to your inhaler device and twist the mouthpiece in a clockwise direction until it is tight. Do not over-tighten.

HOW SUPPLIED

1. Epinephrine Inhalation is a dry powder, USP 0.22 mg, in one number 3 capsule.
2. NDC 15343-104-20, each dose is in an individual capsule. Twenty capsules are packed in one blister. The dry powder in the capsule is in a ready-to-inhale form.

STORAGE AND HANDLING

1. Protect from light
2. Place in a dry area
3. Avoid excessive heat
4. Store between 2°C and 24°C (36°F and 75°F)

INACTIVE INGREDIENT

Lactose

REGULATORY STATUS

OTC Monograph 2013, 21 CFR Part 341.16 and 341.76 Bronchodilator

COMMENTS AND QUESTIONS

1-888-658-8108
Monday through Friday, 8:00 a.m. to 5:00 p.m. (Eastern Standard Time)

Manufactured for: DrNaturalHealing, Inc. 111 McCoy Street Milford, DE 19963, USA Info@DrNaturalHealing.com